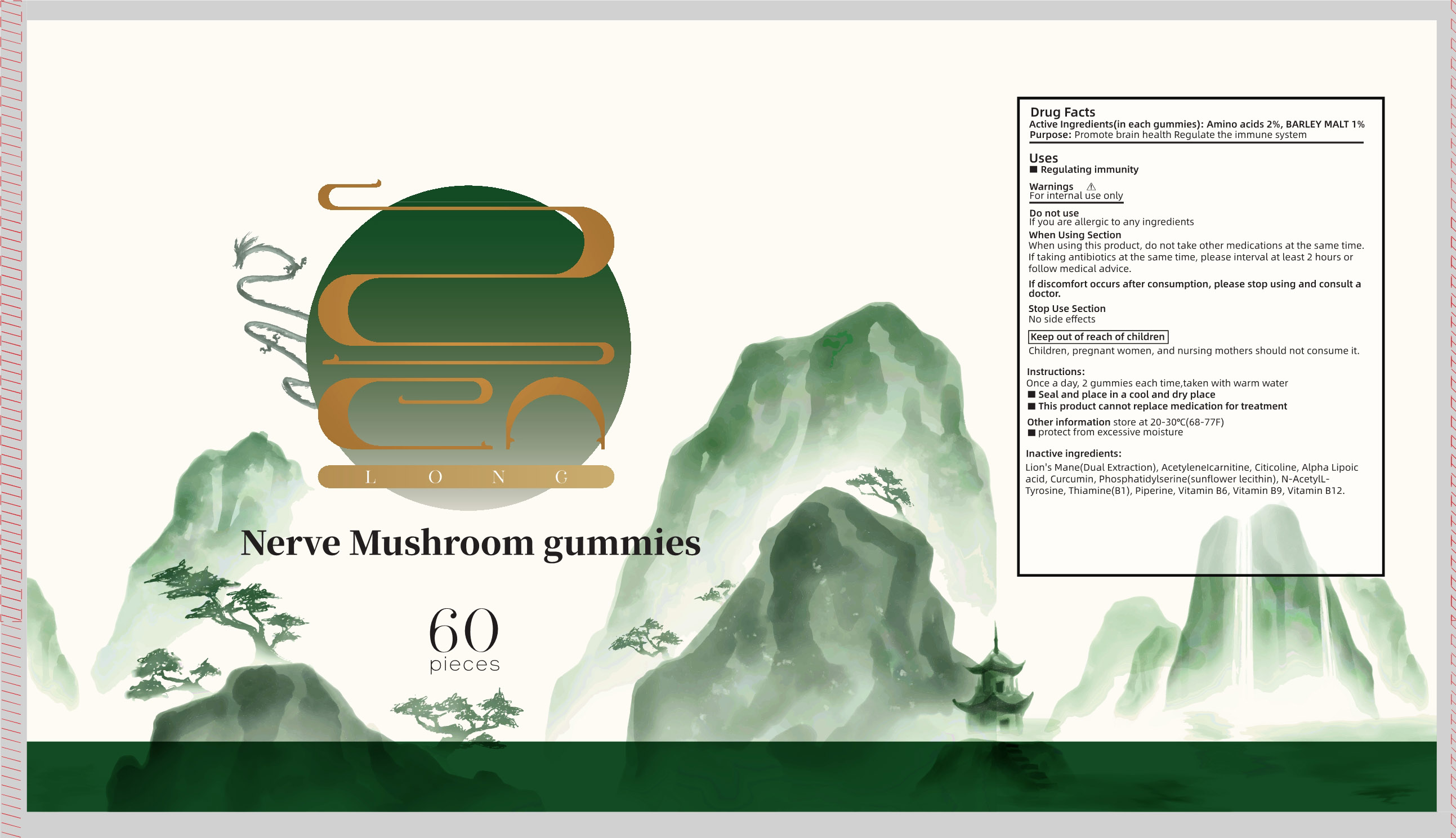 DRUG LABEL: Nerve Mushroom gummies
NDC: 83739-003 | Form: CHEWABLE GEL
Manufacturer: XIAN CHIANG COMPANY LIMITED
Category: otc | Type: HUMAN OTC DRUG LABEL
Date: 20250216

ACTIVE INGREDIENTS: AMINO ACIDS 2 g/100 1; BARLEY MALT 1 g/100 1
INACTIVE INGREDIENTS: PHOSPHATIDYL SERINE; THIAMINE; FOLIC ACID; CYANOCOBALAMIN; PIPERINE; CITICOLINE; ALPHA LIPOIC ACID; PYRIDOXINE; CURCUMIN; HERICIUM ERINACEUS FRUITING BODY; ACETYL L-TYROSINE; ACETYLCARNITINE

83739-003

Active Ingredient

Amino acids 2% , BARLEY MALT 1%

Purpose

Promote brain health Regulate the immune system

Uses

Regulating immunity

Warnings

For internal use only

Do not use

If you are allergic to any ingredients

When Using Section

When using this product , do not take other medications at the same time If taking antibiotics at the same time , please interval at least 2 hours orfollow medical advice.

If discomfort occurs after consumption , please stop using and consult adoctor

Stop Use section

No side effects

Keep out of reach of children

Children , pregnant women , and nursing mothers should not consume it .

Instructions

Once a day , 2 gummies each time , taken with warm water

Seal and place in a cool and dry placem

This product cannot replace medication for treatment

Other information

Other information store at 20-30°C (68-77F)

protect from excessive moisture

Inactive ingredient

Lsion's Mane (Dual Extraction) , Acetylenelcarnitine , Citicoline , Alpha Lipoic acid, Curcumin , Phosphatidylserine (sunflower lecithin) , N-AcetylL-Tyrosine , Thiamine (B1) , Piperine , Vitamin B6 , Vitamin B9 , Vitamin B